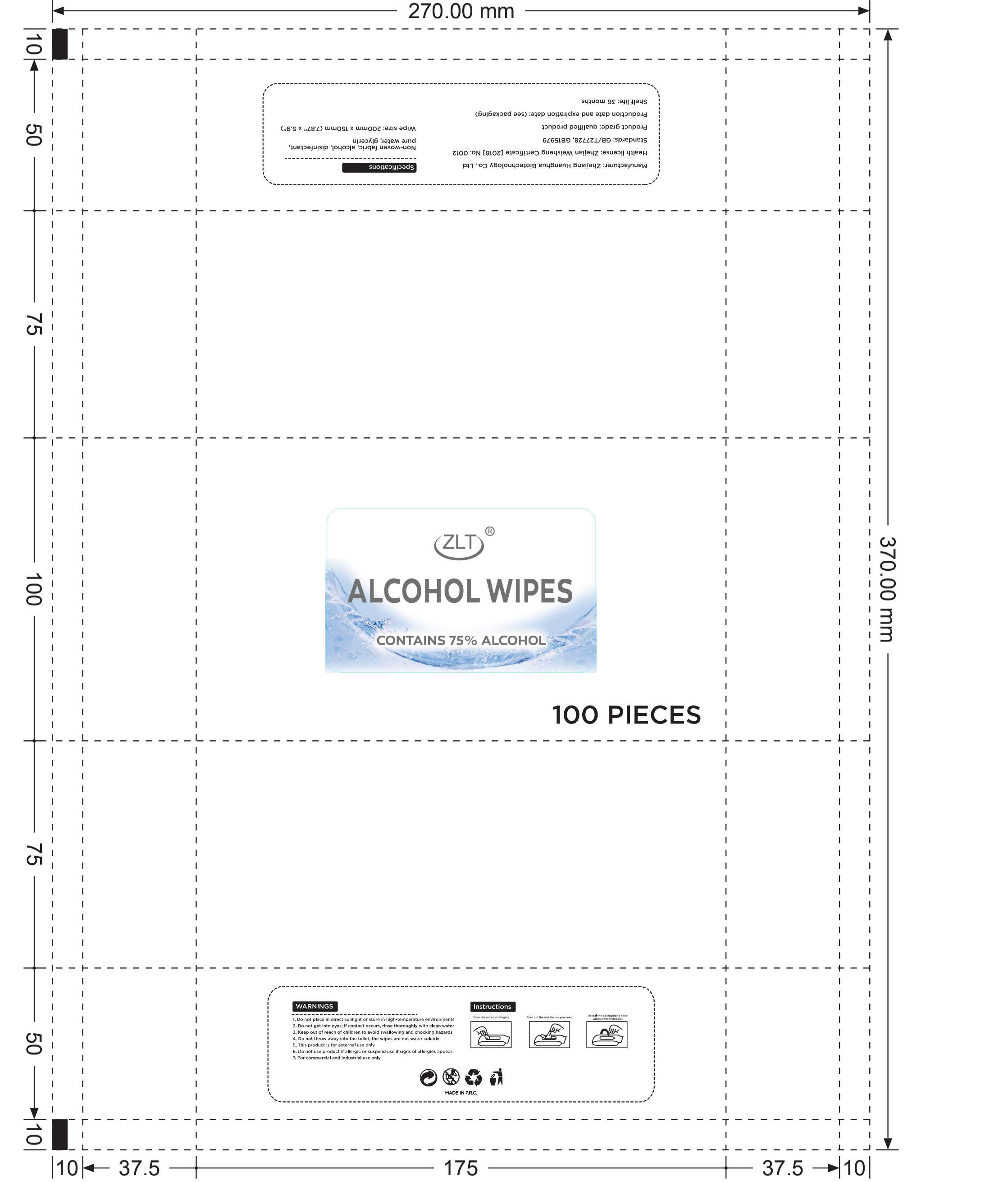 DRUG LABEL: Alcohol wipes
NDC: 41546-012 | Form: CLOTH
Manufacturer: Zhejiang Huanghua Biological Technology Co., Ltd
Category: otc | Type: HUMAN OTC DRUG LABEL
Date: 20201025

ACTIVE INGREDIENTS: ALCOHOL 288 mL/100 1; BENZALKONIUM CHLORIDE 0.5 g/100 1; METHYLISOTHIAZOLINONE 0.5 g/100 1; PROPYLENE GLYCOL 0.5 g/100 1; PHENOXYETHANOL 0.5 g/100 1
INACTIVE INGREDIENTS: WATER

DOSAGE AND ADMINISTRATION

store between 15-30°C(59-86°F),avoid freezing and excessive heat above 40°C(104°F)

INACTIVE INGREDIENT

pure water

INDICATIONS AND USAGE

1.Open cover and remove seal.
2.Pull out wipe corner from center of the roll.
3.Thread through hole in the cover.
4.Close lid after use to retain moisture.

ACTIVE INGREDIENT

alcohol

Benzalkamine

2-methyl-4-isothiazoline-3-one

propylene glyco

2-phenoxyethanol

keep out of reach of children

PURPOSE

Disinfection
Sterilization
No Rinseing

WARNINGS

For external use only. Flammable. Keep away from heat or flame.